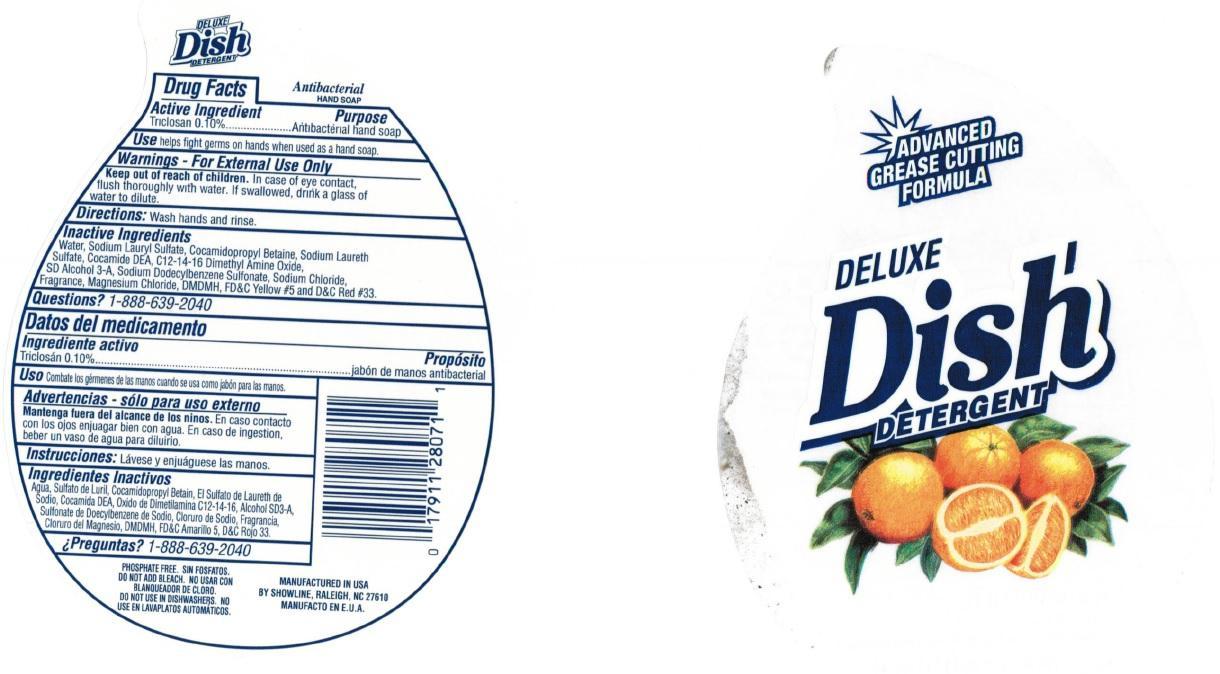 DRUG LABEL: DELUXE Dish DETERGENT
NDC: 53510-000 | Form: SOAP
Manufacturer: Showline, Inc.
Category: otc | Type: HUMAN OTC DRUG LABEL
Date: 20140930

ACTIVE INGREDIENTS: TRICLOSAN 1.0 mg/1 mL
INACTIVE INGREDIENTS: WATER; SODIUM LAURYL SULFATE; COCAMIDOPROPYL BETAINE; SODIUM LAURETH-3 SULFATE; COCO DIETHANOLAMIDE; SODIUM DODECYLBENZENESULFONATE; SODIUM CHLORIDE; MAGNESIUM CHLORIDE; FD&C YELLOW NO. 5; D&C RED NO. 33

DELUXE Dish DETERGENT

Active Ingredient

Triclosan 0.10%

Purpose

Antibacterial hand soap

Use

helps fight germs on hands when used as a hand soap.

Warnings

- For External Use Only

Keep out of reach of children.

In case of eye contact, flush thoroughly with water. If swallowed, drink a glass of water to dilute.

Directions:

Wash hands and rinse.

Inactive Ingredients

Water, Sodium Lauryl Sulfate, Cocamidopropyl Betaine, Sodium Laureth Sulfate, Cocamide DEA, C12-14-16 Dimethyl Amine Oxide, SD Alcohol 3-A, Sodium Dodecylbenzene Sulfonate, Sodium Chloride, Fragrance, Magnesium Chloride, DMDMH, FD&C Yellow #5 and D&C Red #33.

Questions?

1-888-639-2040